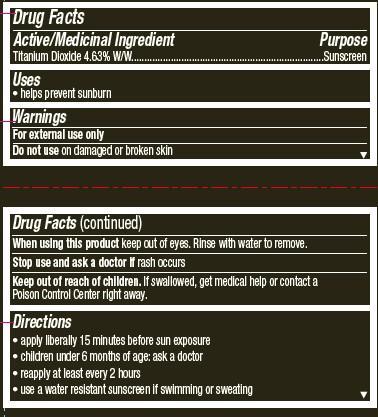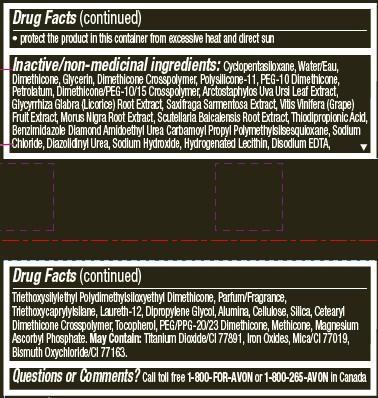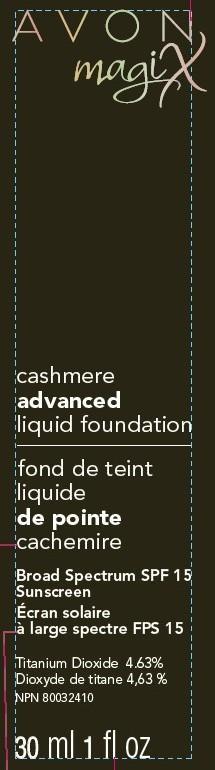 DRUG LABEL: MagixCashmere Advanced
NDC: 10096-0283 | Form: LOTION
Manufacturer: Avon Products, Inc
Category: otc | Type: HUMAN OTC DRUG LABEL
Date: 20120927

ACTIVE INGREDIENTS: Titanium Dioxide 46.3 mg/1 mL

Drug Facts

Active/Medicinal Ingredient
Titanium Dioxide 4.63% W/W...............

Purpose
................................Sunscreen

Uses
• helps prevent sunburn

Warnings

For external use only.

Do not use on damaged or broken skin

When using this product keep out of eyes. Rinse with water to remove.

Stop use and ask a doctor if rash occurs

Keep out of reach of children. If swallowed, get medical help or contact a Poison Control Center right away.

Directions
• apply liberally 15 minutes before sun exposure
• children under 6 months of age: ask a doctor
• reapply at least every 2 hours
• use a water resistant sunscreen if swimming or sweating

• Sun Protection Measures. Spending time in the sun increases your risk of skin cancer and early skin aging. To decrease this risk, regularly use a sunscreen with a Broad Spectrum SPF value of 15 or higher and other sun protection measures including:

• limit time in the sun, especially from 10 a.m. – 2 p.m.
• wear long-sleeved shirts, pants, hats, and sunglasses

Other information

• protect the product in this container from excessive heat and direct sun

INACTIVE INGREDIENT

Inactive/non-medicinal ingredients: Cyclopentasiloxane, Water/Eau, Dimethicone, Glycerin, Dimethicone Crosspolymer, Polysilicone-11, PEG-10 Dimethicone, Petrolatum, Dimethicone/PEG-10/15 Crosspolymer, Arctostaphylos Uva Ursi Leaf Extract, Glycyrrhiza Glabra (Licorice) Root Extract, Saxifraga Sarmentosa Extract, Vitis Vinifera (Grape) Fruit Extract, Morus Nigra Root Extract, Scutellaria Baicalensis Root Extract, Thiodipropionic Acid, Benzimidazole Diamond Amidoethyl Urea Carbamoyl Propyl Polymethylsilsesquioxane, Sodium Chloride, Diazolidinyl Urea, Sodium Hydroxide, Hydrogenated Lecithin, Disodium EDTA,Triethoxysilylethyl Polydimethylsiloxyethyl Dimethicone, Parfum/Fragrance, Triethoxycaprylylsilane, Laureth-12, Dipropylene Glycol, Alumina, Cellulose, Silica, Cetearyl Dimethicone Crosspolymer, Tocopherol, PEG/PPG-20/23 Dimethicone, Methicone, Magnesium Ascorbyl Phosphate. May Contain: Titanium Dioxide/CI 77891, Iron Oxides, Mica/CI 77019, Bismuth Oxychloride/CI 77163.

Questions or Comments? Call toll free 1-800-FOR-AVON or 1-800-265-AVON in Canada